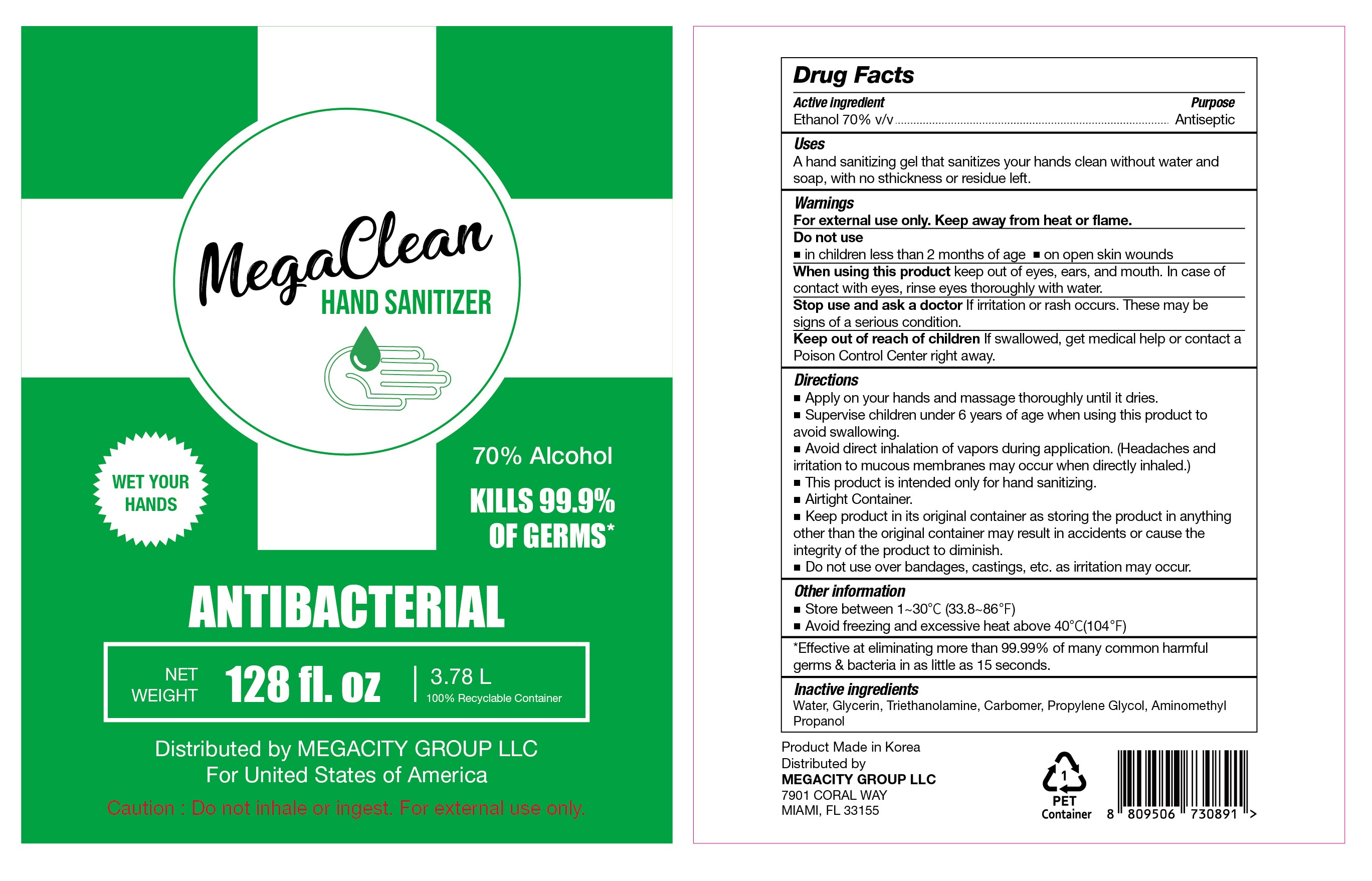 DRUG LABEL: MegaClean HAND SANITIZER
NDC: 77799-001 | Form: GEL
Manufacturer: MEGACITY GROUP LLC
Category: otc | Type: HUMAN OTC DRUG LABEL
Date: 20200531

ACTIVE INGREDIENTS: ALCOHOL 2646 mL/3780 mL
INACTIVE INGREDIENTS: AMINOMETHYLPROPANOL; GLYCERIN; WATER; PROPYLENE GLYCOL; TROLAMINE; CARBOMER HOMOPOLYMER, UNSPECIFIED TYPE

MegaClean HAND SANITIZER 1 Gallon Gel type
77799-001-01